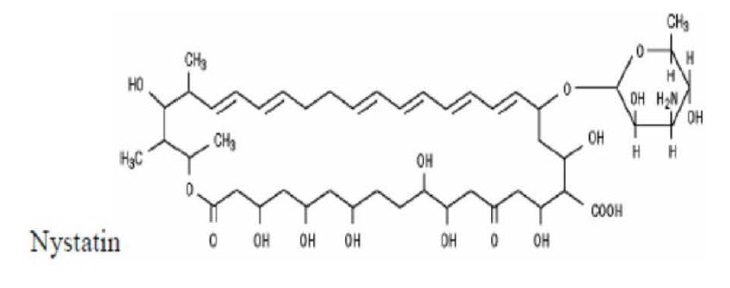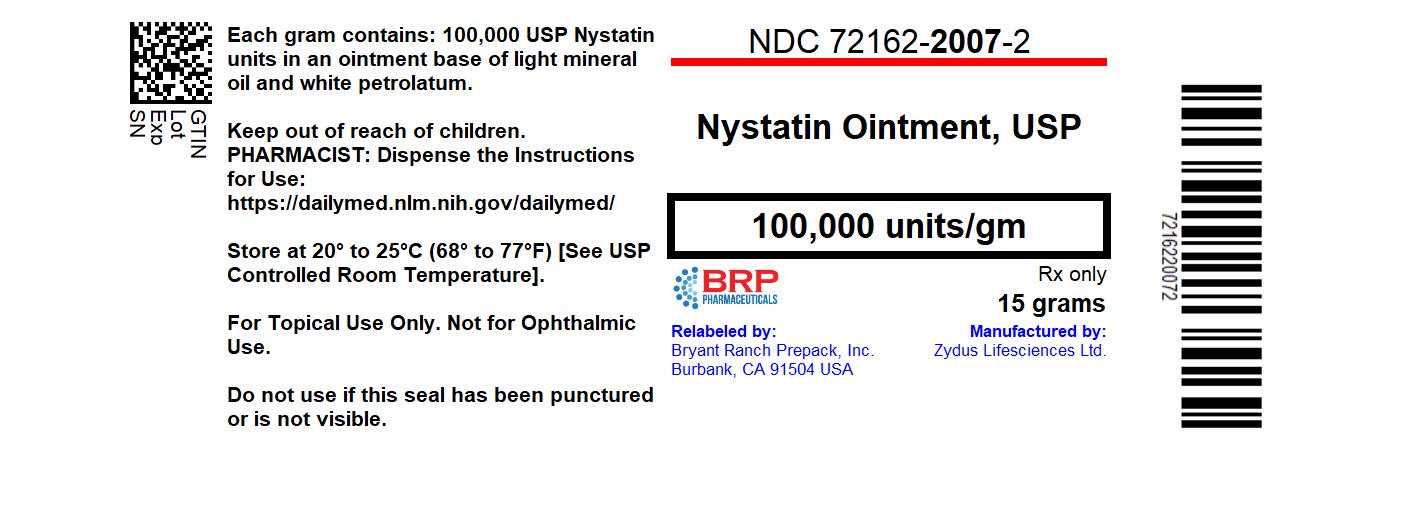 DRUG LABEL: Nystatin
NDC: 72162-2007 | Form: OINTMENT
Manufacturer: Bryant Ranch Prepack
Category: prescription | Type: HUMAN PRESCRIPTION DRUG LABEL
Date: 20240326

ACTIVE INGREDIENTS: NYSTATIN 100000 U/1 g
INACTIVE INGREDIENTS: MINERAL OIL; PETROLATUM

Nystatin Ointment, USP

DESCRIPTION

Nystatin is a polyene antifungal antibiotic drug obtained from Streptomyces nursei.

Structural formula:

Nystatin Ointment is for dermatologic use. Nystatin Ointment USP, for topical use only, contains 100,000 USP Nystatin Units per gram, in a white petrolatum and light mineral oil base.

CLINICAL PHARMACOLOGY

Pharmacokinetics

Nystatin is not absorbed from intact skin or mucous membrane.

Microbiology

Nystatin is an antibiotic which is both fungistatic and fungicidal in vitro against a wide variety of yeasts and yeast-like fungi, including Candida albicans, C.parapsilosis, C.tropicalis, C.guilliermondi, C. pseudotropicalis, C. krusei, Torulopsis glabrata, Tricophyton rubrum, T. mentagrophytes.

Nystatin acts by binding to sterols in the cell membrane of susceptible species resulting in a change in membrane permeability and the subsequent leakage of intracellular components. On repeated subculturing with increasing concentrations of nystatin, Candida albicans does not develop resistance to nystatin. Generally, resistance to nystatin does not develop during therapy. However, other species of Candida (C. tropicalis, C. guilliermondi, C. krusei, and C. stellatoides) become quite resistant on treatment with nystatin and simultaneously become cross resistant to amphotericin as well. This resistance is lost when the antibiotic is removed.

Nystatin exhibits no appreciable activity against bacteria, protozoa, or viruses.

INDICATIONS AND USAGE

Nystatin Ointment is indicated in the treatment of cutaneous or mucocutaneous mycotic infections caused by Candida albicans and other susceptible Candida species.

Nystatin Ointment is not indicated for systemic, oral, intravaginal or ophthalmic use.

CONTRAINDICATIONS

Nystatin Ointment is contraindicated in patients with a history of hypersensitivity to any of their components.

PRECAUTIONS

General

Nystatin Ointment should not be used for the treatment of systemic, oral, intravaginal or ophthalmic infections.

If irritation or sensitization develops, treatment should be discontinued and appropriate measures taken as indicated. It is recommended that KOH smears, cultures, or other diagnostic methods be used to confirm the diagnosis of cutaneous or mucocutaneous candidiasis and to rule out infection caused by other pathogens.

INFORMATION FOR PATIENTS

Patients using these medications should receive the following information and instructions:

1. The patient should be instructed to use these medications as directed (including the replacement of missed doses). These medications are not for any disorder other than that for which they are prescribed.
2. Even if symptomatic relief occurs within the first few days of treatment, the patient should be advised not to interrupt or discontinue therapy until the prescribed course of treatment is completed.
3. If symptoms of irritation develop, the patient should be advised to notify the physician promptly

Laboratory Tests

If there is a lack of therapeutic response, KOH smears, cultures, or other diagnostic methods should be repeated.

Carcinogenesis, Mutagenesis, Impairment of Fertility

No long-term animal studies have been performed to evaluate the carcinogenic potential of nystatin. No studies have been performed to determine the mutagenicity of nystatin or its effects on male or female fertility.

Pregnancy: Teratogenic Effects

Category C.

Animal reproduction studies have not been conducted with any nystatin topical preparation. It also is not known whether these preparations can cause fetal harm when used by a pregnant woman or can affect reproductive capacity. Nystatin topical preparations should be prescribed for a pregnant woman only if the potential benefit to the mother outweighs the potential risk to the fetus.

Nursing Mothers

It is not known whether nystatin is excreted in human milk. Caution should be exercised when nystatin is prescribed for a nursing woman.

Pediatric Use

Safety and effectiveness have been established in the pediatric population from birth to 16 years.

See DOSAGE AND ADMINISTRATION

ADVERSE REACTIONS

The frequency of adverse events reported in patients using Nystatin Ointment preparations is less than 0.1%. The more common events that were reported include allergic reactions, burning, itching, rash, eczema, and pain on application.

(See PRECAUTIONS: General.)

DOSAGE AND ADMINISTRATION

NYSTATIN Ointment

Adults and Pediatric Patients (Neonates and Older):

Apply liberally to affected areas twice daily or as indicated until healing is complete.

HOW SUPPLIED

NDC: 72162-2007-2: 15 grams in a TUBE

NDC: 72162-2007-3: 30 grams in a TUBE

NYSTATIN Ointment: Store at room temperature.

Call your doctor for medical advice about side effects. You may report side effects to Viona Pharmaceuticals Inc. at 1-888-304-5011 or FDA at 1-800-FDA-1088.

Repackaged/Relabeled by:

Bryant Ranch Prepack, Inc.

Burbank, CA 91504

STORAGE

NYSTATIN Ointment: Store at room temperature.

Call your doctor for medical advice about side effects. You may report side effects to Viona Pharmaceuticals Inc. at 1-888-304-5011 or FDA at 1-800-FDA-1088.

Manufactured by:

Zydus Lifesciences Ltd.

Changodar, Ahmedabad, India.

Distributed by:

Viona Pharmaceuticals Inc.

Cranford, NJ 07016

Rev.: 06/22

PACKAGE LABEL

Nystatin 100,000u/g Oint, USP #15